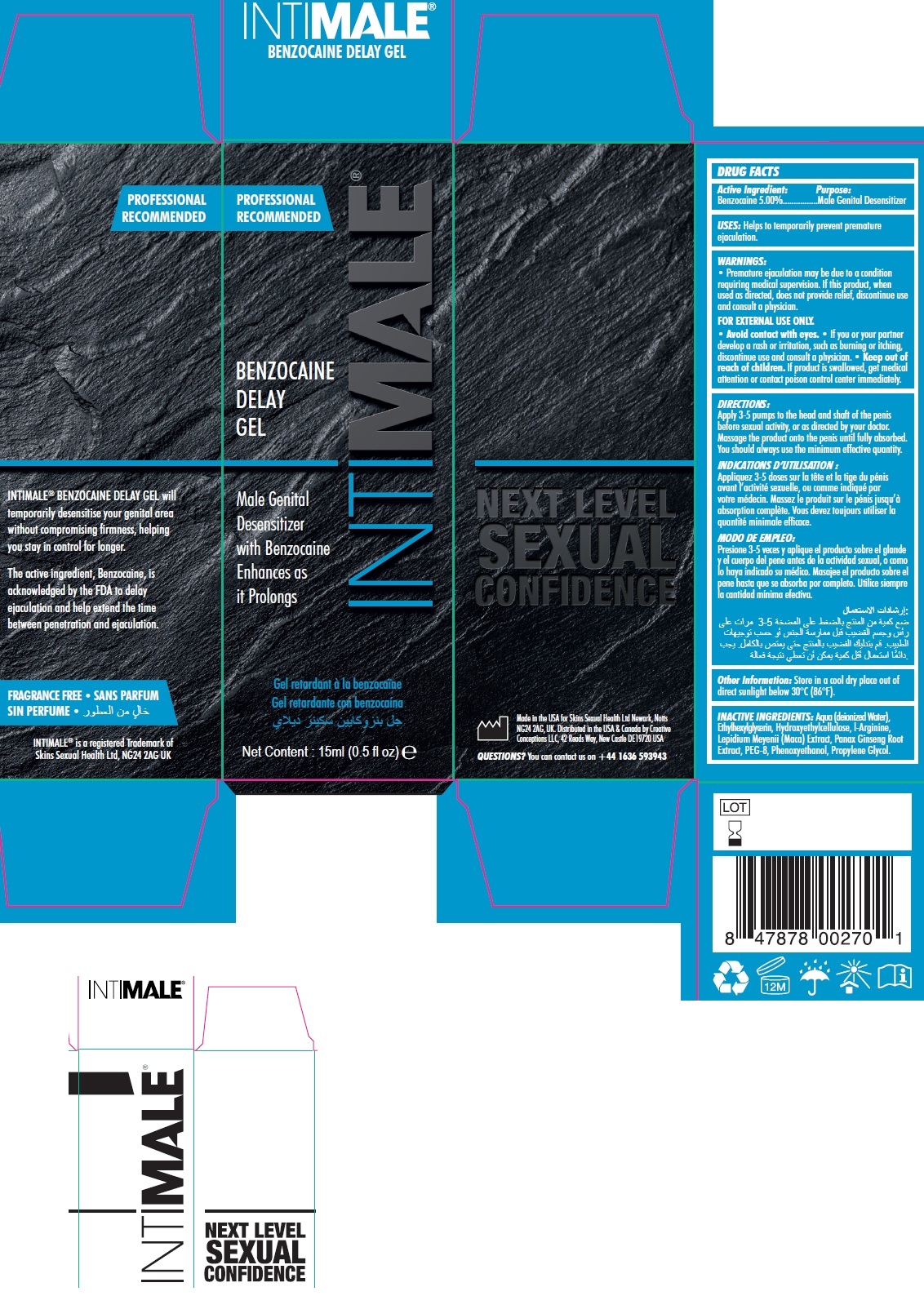 DRUG LABEL: INTIMALE Benzocaine Delay Gel
NDC: 81923-369 | Form: GEL
Manufacturer: SKINS SEXUAL HEALTH LIMITED
Category: otc | Type: HUMAN OTC DRUG LABEL
Date: 20231106

ACTIVE INGREDIENTS: BENZOCAINE 50 mg/1 mL
INACTIVE INGREDIENTS: ALOE VERA LEAF; ETHYLHEXYLGLYCERIN; HYDROXYETHYL CELLULOSE, UNSPECIFIED; ARGININE; ASIAN GINSENG; POLYETHYLENE GLYCOL 400; PHENOXYETHANOL; PROPYLENE GLYCOL

INTIMALE Benzocaine Delay Gel

ACTIVE INGREDIENT:

Benzocaine 5.00%

Purpose:

Male Genital Desensitizer

USES:

Helps to temporarily prevent premature ejaculation.

WARNINGS:

• Premature ejaculation may be due to a condition requiring medical supervision. If this product, when used as directed, does not provide relief, discontinue use and consult a physician. If you or your partner develop a rash or irritation, such as burning or itching, discontinue use and consult a physician.
FOR EXTERNAL USE ONLY.• Avoid contact with eyes.

Keep out of reach of children.

If product is swallowed, get medical attention or contact poison control center immediately.

DIRECTIONS:

Apply 3-5 pumps to the head and shaft of the penis before sexual activity, or as directed by your doctor. Massage the product onto the penis until fully absorbedOther Information:. You should always use the minimum effective quantity.

Other Information:

Store in a cool dry place out of direct sunlight below 30°C (86°F).

INACTIVE INGREDIENTS:

Aqua (deionized Water), Ethylhexylglycerin, Hydroxyethylcellulose, l-Arginine, Lepidium Meyenii (Maca) Extract, Panax Ginseng Root Extract, PEG-8, Phenoxyethanol, Propylene Glycol.

QUESTIONS?

You can contact us on +44 1636 593943